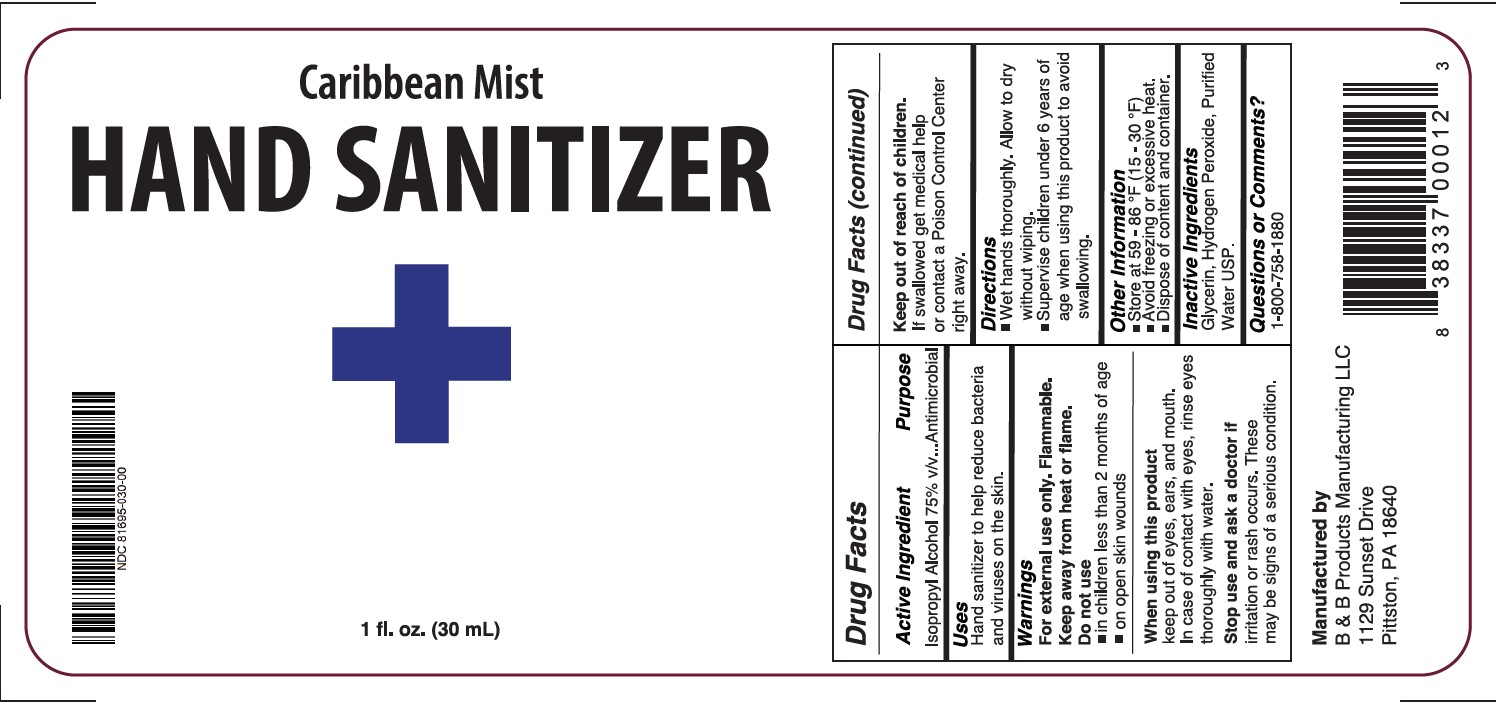 DRUG LABEL: CARIBBEAN MIST HAND SANITIZER
NDC: 81695-030 | Form: GEL
Manufacturer: B & B PRODUCTS MANUFACTURING LLC
Category: otc | Type: HUMAN OTC DRUG LABEL
Date: 20210322

ACTIVE INGREDIENTS: ISOPROPYL ALCOHOL 75 mL/100 mL
INACTIVE INGREDIENTS: HYDROGEN PEROXIDE; GLYCERIN; WATER

CARIBBEAN MIST HAND SANITIZER 30 mL

ACTIVE INGREDIENT

Isopropyl Alcohol 75%

PURPOSE

Antimicrobial

USES

Hand sanitizer to help reduce bacteria that potentially can cause disease.

WARNINGS

For external use only. Flammable. Keep away from heat or flame

Do not use

■ in children less than 2 months of age

■ on open skin wounds

When using this product keep out of eyes, ears, and mouth. In case of contact with eyes, rinse eyes thoroughly with water.

Stop use and ask a doctor if irritation or rash occurs. These may be signs of a serious condition.

Keep out of reach of children. If swallowed, get medical help or contact a Poison Control Center right away.

Keep out of reach of children If swallowed get medical help or contact a Poison Control Center right away.

DIRECTIONS

■ Place enough product on hands to cover all surfaces. Rub hands together until dry.

■ Supervise children under 6 years of age when using this product to avoid swallowing.

OTHER INFORMATION

■ Store between 15-30C (59-86F)

■ Avoid freezing and excessive heat above 40C (104F)

INACTIVE INGREDIENTS

Glycerin, Hydrogen Peroxide, Purified Water USP.

QUESTIONS OR COMMENTS?

1-800-758-1880.